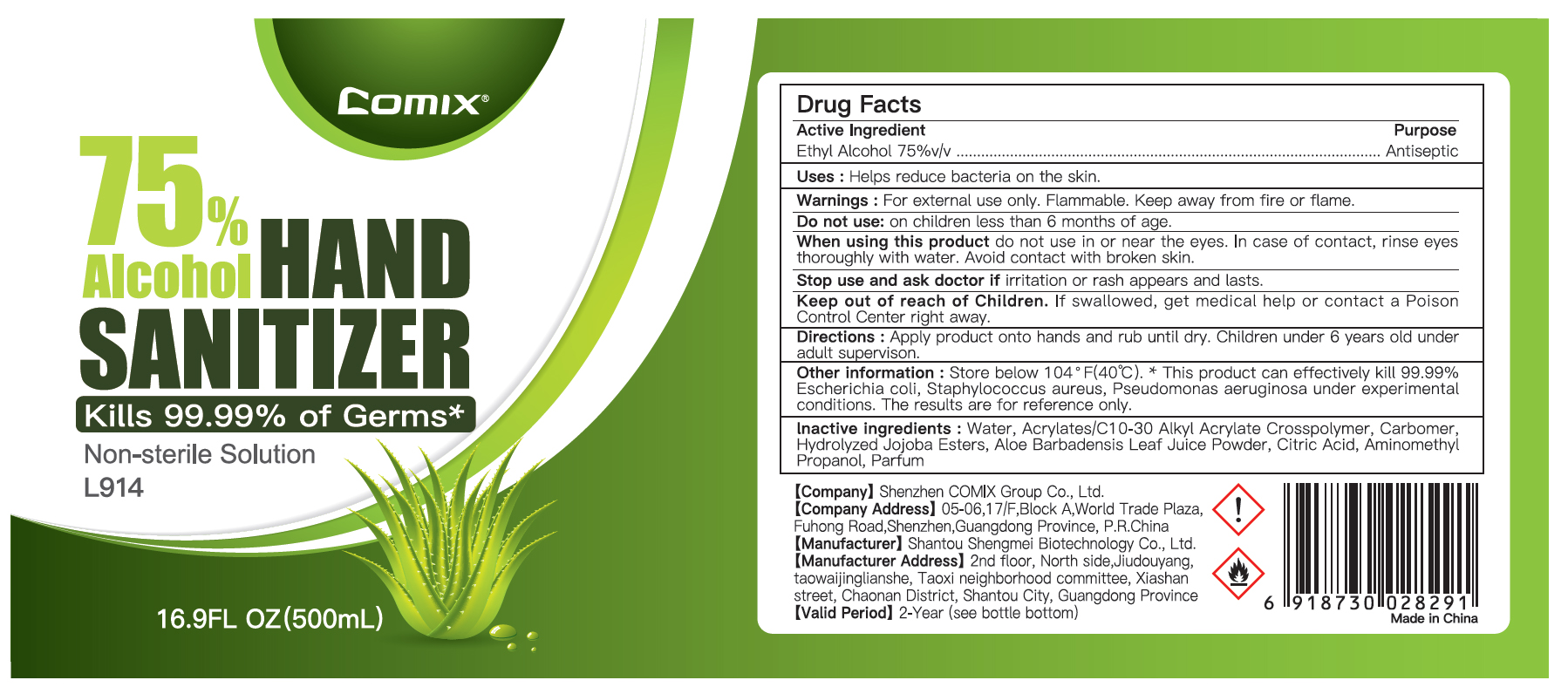 DRUG LABEL: Comix Alcohol Hand Sanitizer
NDC: 55450-010 | Form: GEL
Manufacturer: Shantou Shengmei Biotechnology Co., Ltd.
Category: otc | Type: HUMAN OTC DRUG LABEL
Date: 20200820

ACTIVE INGREDIENTS: ALCOHOL 75 mL/100 mL
INACTIVE INGREDIENTS: CARBOMER HOMOPOLYMER, UNSPECIFIED TYPE; HYDROLYZED JOJOBA ESTERS (ACID FORM); CARBOMER INTERPOLYMER TYPE A (ALLYL SUCROSE CROSSLINKED); ALOE VERA LEAF; CITRIC ACID MONOHYDRATE; WATER; AMINOMETHYLPROPANOL

Comix Alcohol Hand Sanitizer

Active Ingredient

Ethyl Alcohol 75% v/v. Purpose: Antiseptic

Purpose

Antiseptic, Hand Sanitizer

Uses

Helps reduce bacteria on the skin

Warnings

For external use only. Flammable. Keep away from heat or flame.

Do not use

on children less than 6 months of age

When using this product

do not use in or near the eyes. In case of contact with eyes, rinse eyes thoroughly with water. Avoid contact with broken skin.

Stop use and ask doctor

if irritation or rash appears and lasts.

Keep out of reach of children.

If swallowed, get medical help or contact a Poison Control Center right away.

Directions

Apply product onto hands and rub until dry. Children under 6 years old under adult supervision.

Other information

Store below 105F (40F). * This product can effectively kill 99.99% Escherichia coli, Staphylococcus aureus, Candida albicans, Pseudomonas aeruginosa under experimental conditions. These results are for reference only.

Inactive ingredients

Water, Acrylates/C10-30 Alkyl Acrylate Crosspolymer, Carbomer, Parfum, Aminomethyl Propanol, Hydrolyzed Jojoba Esters, Aloe Barbadensis Leaf Juice Powder, Citric Acid

PACKAGE LABEL

55450-010-01 500mL

Comix

75% Alcohol

HAND

SANITIZER

Kills 99.99% of Germs*

Non-sterile Solution

L914

16.9FL OZ (500mL)